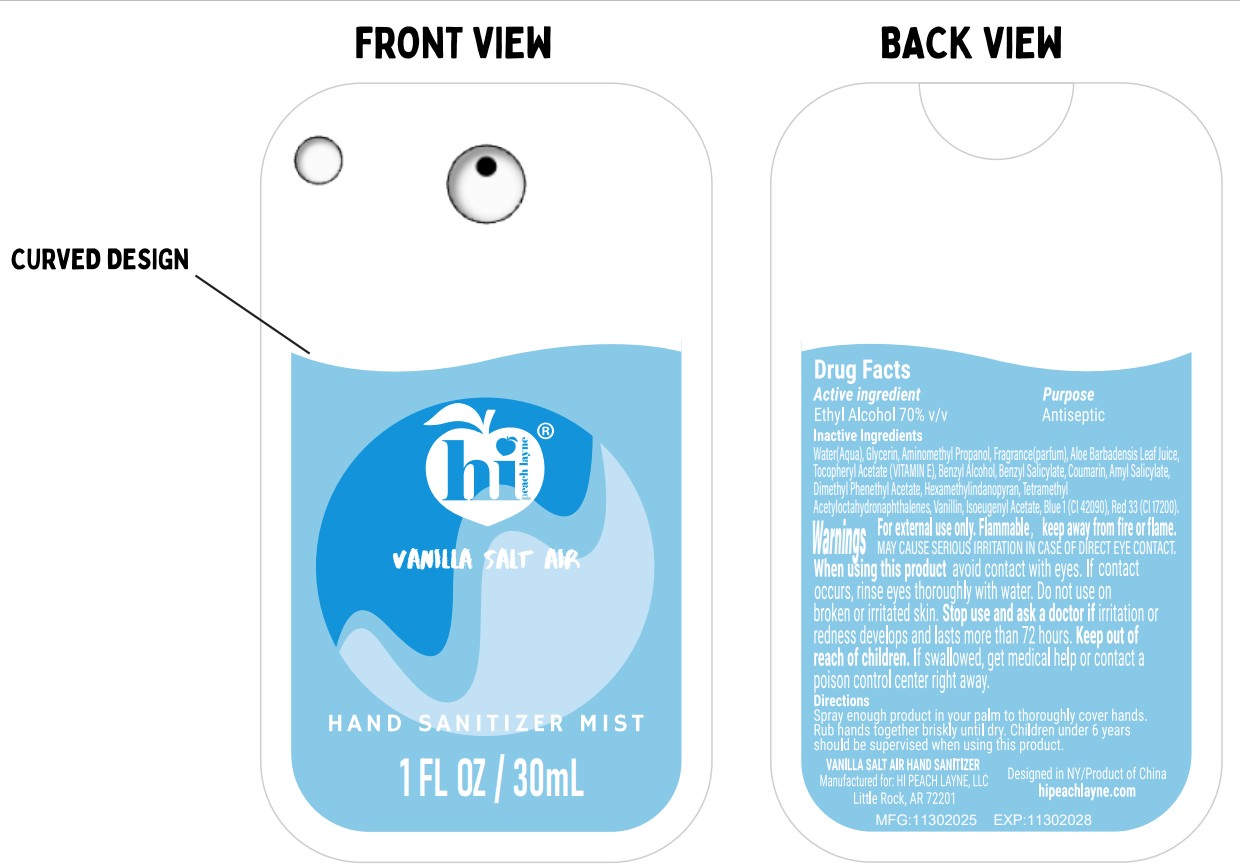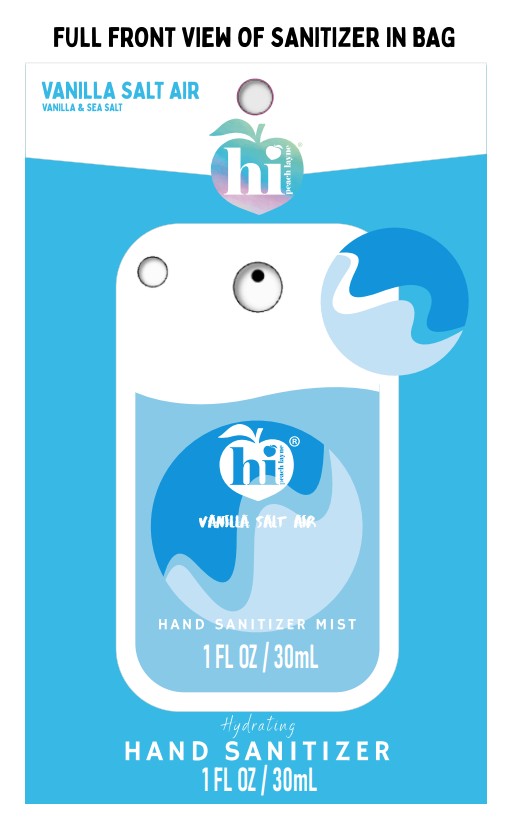 DRUG LABEL: hi peach layne
NDC: 73905-049 | Form: SPRAY
Manufacturer: Zhejiang Jinghui Cosmetics Share Co., Ltd.
Category: otc | Type: HUMAN OTC DRUG LABEL
Date: 20260116

ACTIVE INGREDIENTS: ALCOHOL 70 mL/100 mL
INACTIVE INGREDIENTS: COUMARIN; VANILLIN; AMINOMETHYL PROPANOL; FRAGRANCE 13576; DIMETHYL BENZYL CARBINYL ACETATE; BLUE 1; RED 33; BENZYL SALICYLATE; WATER; ALPHA-TOCOPHEROL ACETATE; BENZYL ALCOHOL; ISOEUGENYL ACETATE; AMYL SALICYLATE; HEXAMETHYLINDANOPYRAN; GLYCERIN; TETRAMETHYL ACETYLOCTAHYDRONAPHTHALENES; ALOE BARBADENSIS LEAF JUICE

3- VANILLA SALT AIR HAND SANITIZER-73905-049-30ml

ACTIVE INGREDIENT

Ethyl Alcohol 70% v/v

PURPOSE

Antiseptic

INACTIVE INGREDIENT

Water(Aqua), Glycerin, Aminomethyl Propanol, Fragrance(parfum), Aloe Barbadensis Leaf Juice, Tocopheryl Acetate (VITAMIN E), BenzyI Alcohol, Benzyl Salicylate, Coumarin, AmyI Salicylate, Dimethyl Phenethyl Acetate, Hexamethylindanopyran, Tetramethyl Acetyloctahydronaphthalenes, Vanillin, lsoeugenyl, Acetate, Blue 1(CI 42090), Red 33(CI 17200)

WARNINGS

For external use only. Flammable, keep away from fire or flame.

MAY CAUSE SERIOUS IRRITATION IN CASE OF DIRECT EYE CONTACT.When using this product avoid contact with eyes. If contact occurs, rinse eyes thoroughly with water. Do not use on broken or irritated skin. Stop use and ask a doctor if irritation or redness develops and lasts more than 72 hours.

Keep out of reach of children.If swallowed,get medical help or contact a poison control center right away.

INDICATIONS AND USAGE

Spray enough product in your palm to thoroughly cover hands. Rub hands together briskly until dry. Children under 6 years should be supervised when using this product.

DOSAGE AND ADMINISTRATION

Spray enough product in your palm to thoroughly cover hands. Rub hands together briskly until dry.